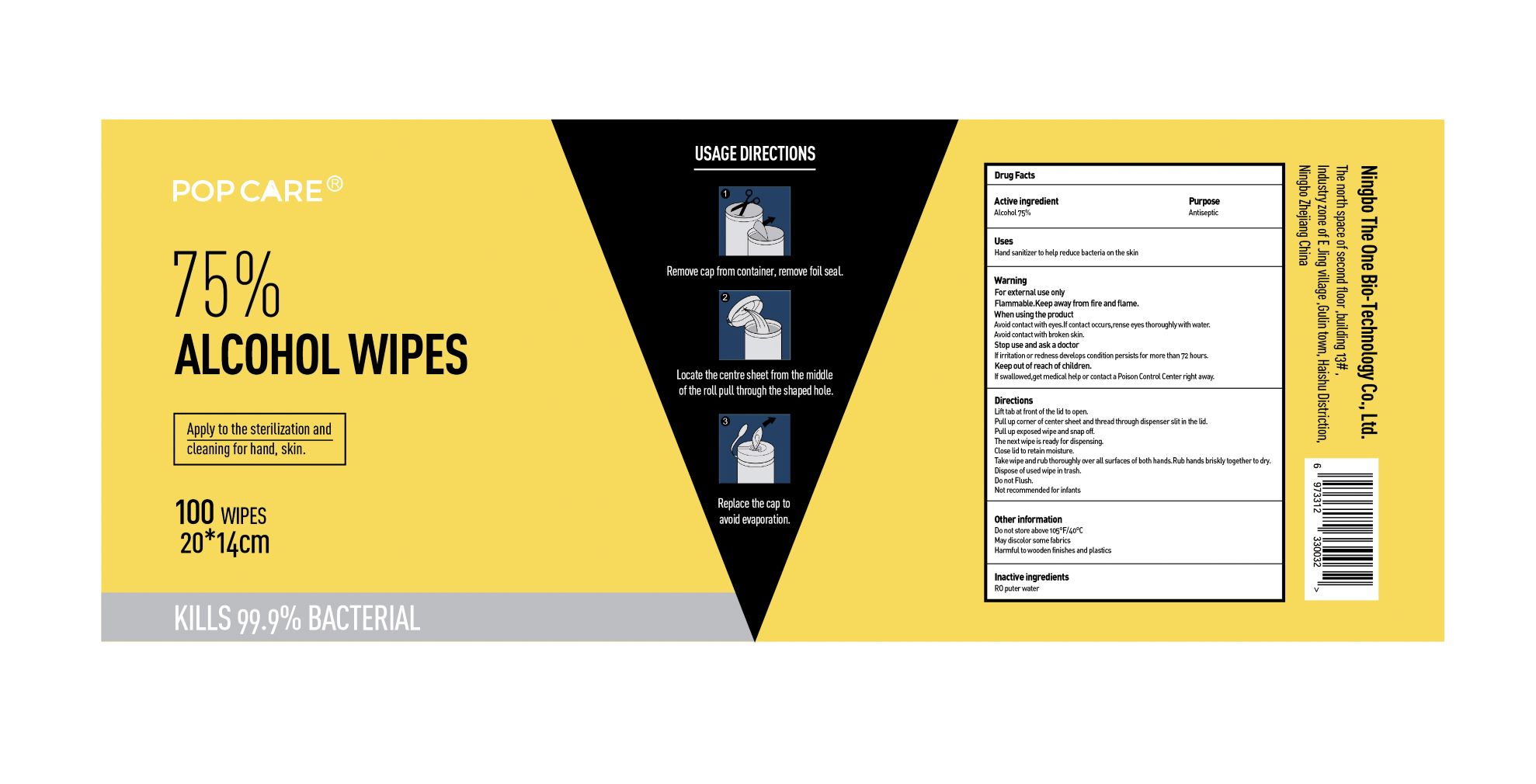 DRUG LABEL: PopCare
NDC: 81478-001 | Form: CLOTH
Manufacturer: Ningbo The One Bio-technology Co., Ltd
Category: otc | Type: HUMAN OTC DRUG LABEL
Date: 20210127

ACTIVE INGREDIENTS: ALCOHOL 75 mL/100 mL
INACTIVE INGREDIENTS: WATER

PopCare

Active Ingredient(s)

Alcohol 75% Purpose: Antiseptic

Purpose

Antiseptic

Use

Hand sanitizer to help reduce bacteria on the skin.

Warnings

For external use only. Flammable. Keep away from heat or flame

When using the product

Avoid contact with eyes. If contact occurs, rinse eyes thoroughly with water.

Avoid contact with broken skin.

Stop use and ask a doctor

if irritation or redness develops condition persists for more than 72 hours.

Keep out of reach of children. If swallowed, get medical help or contact a Poison Control Center right away.

Directions

Lift tab at front of the lid to open.

Pull up corner of center sheet and thread through dispenser slit in the lid.

Pull up exposed wipe and snap off.

The next wipe is ready for dispensing.

Close lid to retaining moisture. T

ake wipe and rub thoroughly over all surfaces of both hands. Rub hands briskly together to dry.

Dispose of used wipe in trash.

Do not Flush.

Not recommended for infants

Other information

Do not store above 105F/40C

May discolor some fabrics

Harmful to wooden finishes and plastics

Inactive ingredients

R0 puter water